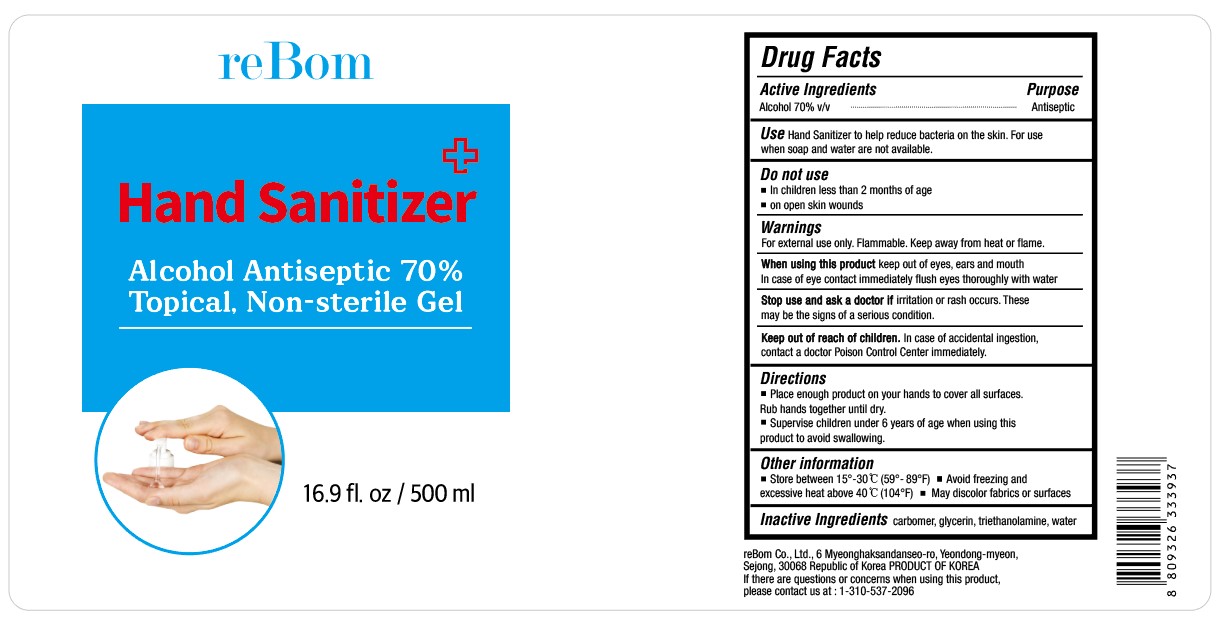 DRUG LABEL: Hand Sanitizer
NDC: 60604-010 | Form: GEL
Manufacturer: reBom Co., Ltd.
Category: otc | Type: HUMAN OTC DRUG LABEL
Date: 20200413

ACTIVE INGREDIENTS: ALCOHOL 70 mL/100 mL
INACTIVE INGREDIENTS: GLYCERIN; TROLAMINE; WATER; CARBOMER HOMOPOLYMER, UNSPECIFIED TYPE

reBom Hand Sanitizer

Active Ingredient

Alcohol 70% v/v

Purpose

Antiseptic

Use

Hand Sanitizer to help decrease bacteria on the skin. For use when soap and water are not available.

Do not use

■ In children less than 2 months of age

■ on open skin wounds

Warnings

For external use only. Flammable. Keep away from heat or flame.

When using this product

Keep out of eyes ears an mouth . In case of eye contact immediately flush eyes throughly with water

Stop use and ask a doctor if

irritation or rash occurs. These may be signs of a serious condition

Keep out of reach of children

In case of accidental ingestion, contact a doctor or Poison Control Center immediately.

Directions

■ Place enough product on your hands to cover all surfaces. Rub hands together until dry ■ Supervise children under 6 years of age when using this product to aviod swallowing.

Other information

■ Store between 15º-30ºC (59º-89ºF) ■ Avoid freezing and excessive heat above 40ºC (140ºF) ■ May discolor fabrics or surfaces

Inactive Ingredients

carbomer, glycerin, triethanolamine, water